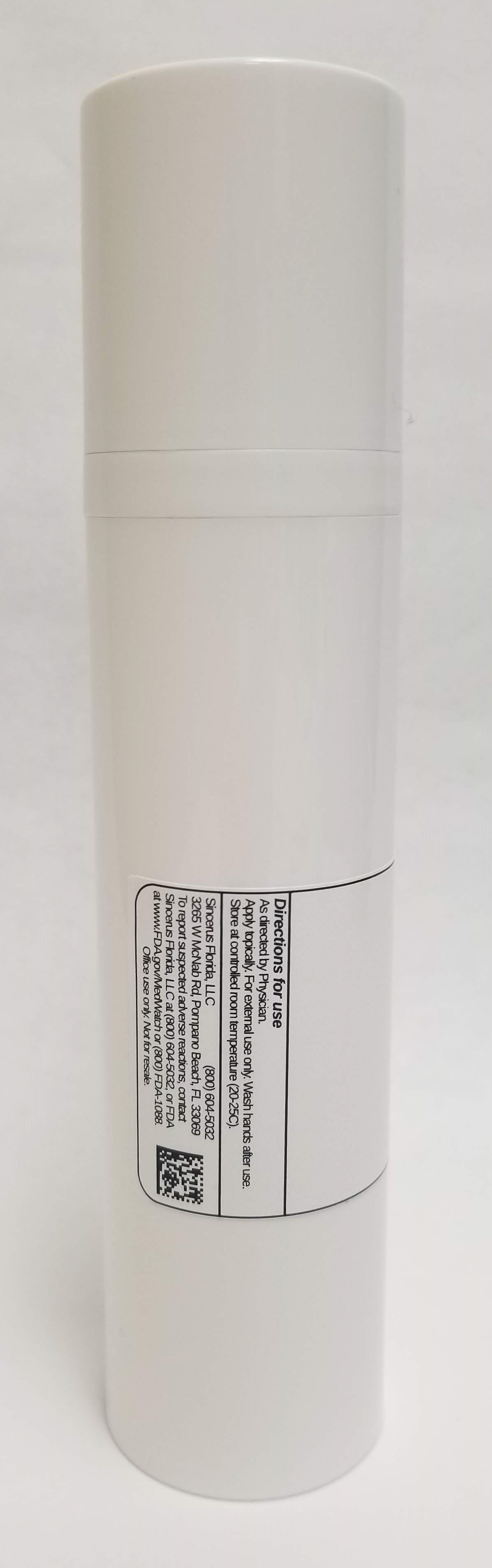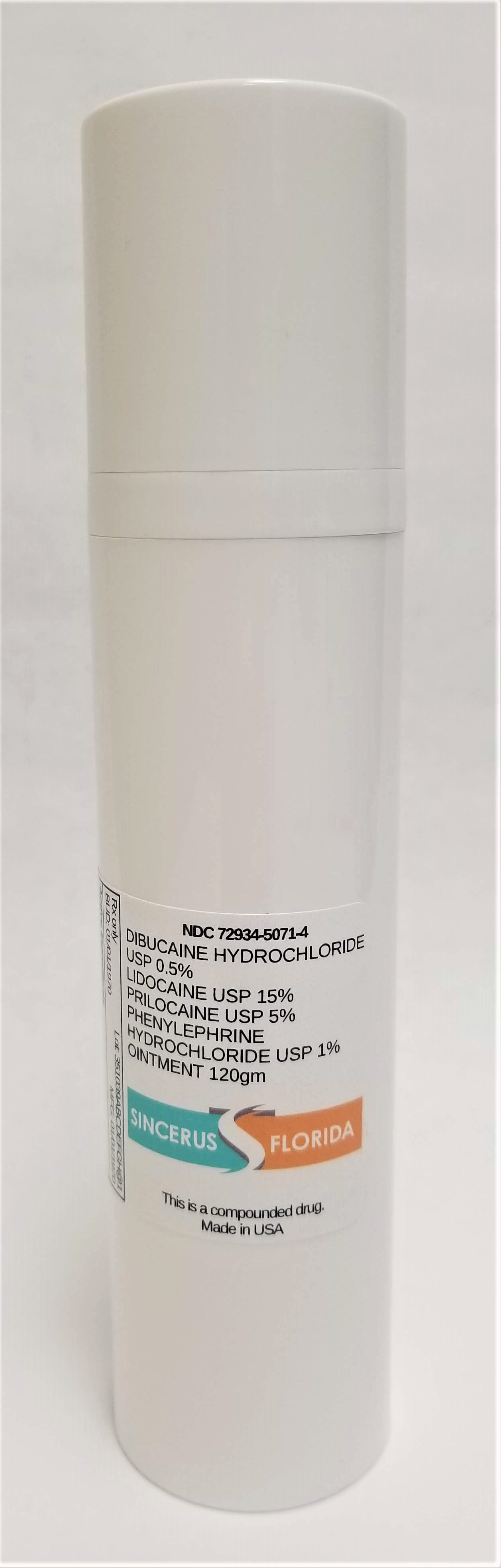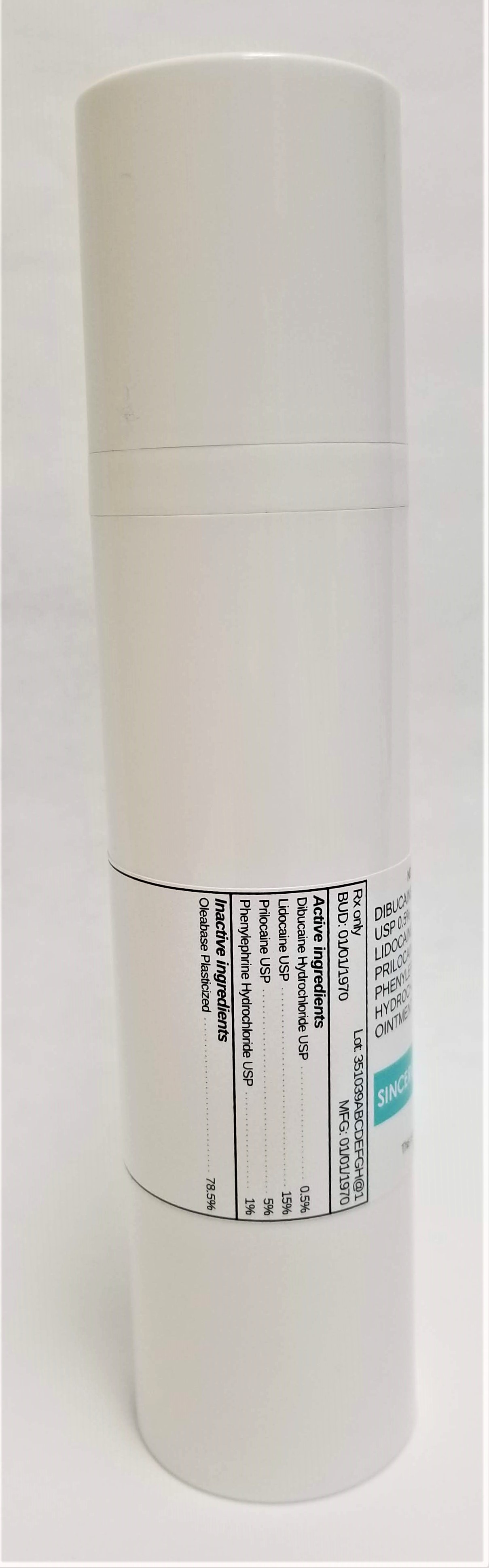 DRUG LABEL: DIBUCAINE HCL 0.5% / LIDOCAINE 15% / PHENYLEPHRINE HCL 1% / PRILOCAINE 5%
NDC: 72934-5071 | Form: OINTMENT
Manufacturer: Sincerus Florida, LLC
Category: prescription | Type: HUMAN PRESCRIPTION DRUG LABEL
Date: 20190510

ACTIVE INGREDIENTS: DIBUCAINE HYDROCHLORIDE 0.5 g/100 g; PHENYLEPHRINE HYDROCHLORIDE 1 g/100 g; LIDOCAINE 15 g/100 g; PRILOCAINE 5 g/100 g

DIBUCAINE HCL 0.5% / LIDOCAINE 15% / PHENYLEPHRINE HCL 1% / PRILOCAINE 5%